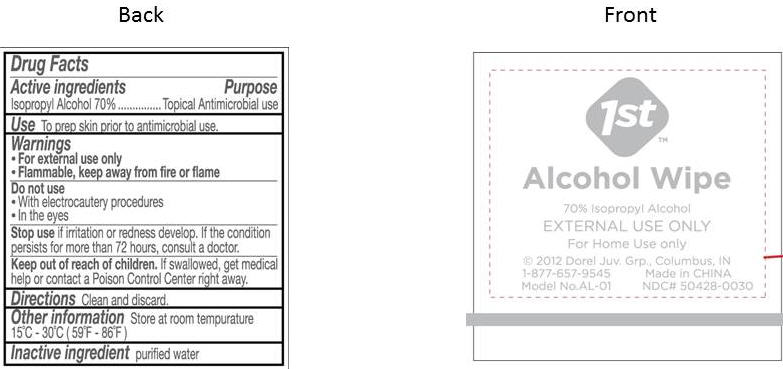 DRUG LABEL: Alcohol Wipe
NDC: 50428-0030 | Form: SWAB
Manufacturer: Dorel Juvenile Group
Category: otc | Type: HUMAN OTC DRUG LABEL
Date: 20131031

ACTIVE INGREDIENTS: ISOPROPYL ALCOHOL .70 mL/1 1
INACTIVE INGREDIENTS: WATER

1st™ Alcohol Wipe 70% Isopropyl Alcohol

Active ingredients

Isopropyl Alcohol 70%

Purpose

Topical Antimicrobial use

Use

To prep skin prior to antimicrobial use.

Warnings

- For external use only
- Flammable, keep away from fire or flame

Do not use

- With electrocautery procedures
- In the eyes

Stop use

if irritation or redness develop. If the condition persists for more than 72 hours, consult a doctor.

Keep out of reach of children.

If swallowed, get medical help or contact a Poison Control Center right away.

Directions

Clean and discard.

Other information

Store at room temperature 15°C - 30°C (59°F - 86°F)

Inactive ingredients

purified water

Package/Label Principal Display Panel

1st™ Alcohol Wipe

70% Isopropyl Alcohol

EXTERNAL USE ONLY

For Home Use only

© 2012 Dorel Juv. Grp., Columbus, IN
1-877-657-9545 Made in CHINA
Model No. AL-01 NDC# 50428-0030

Package Label